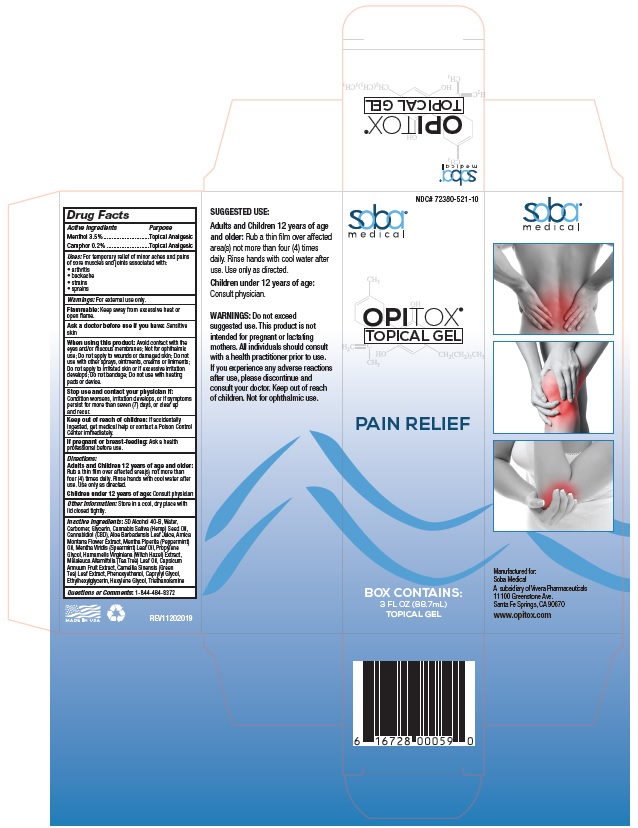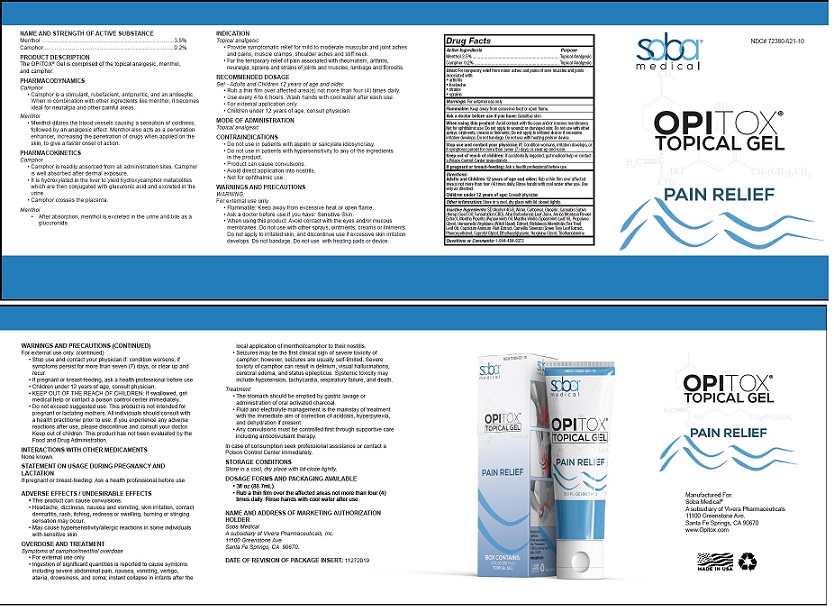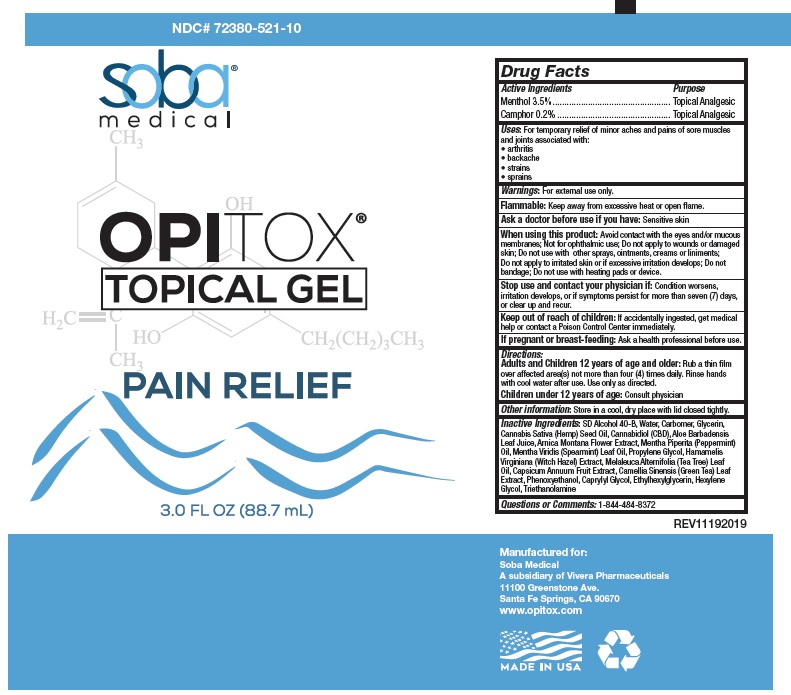 DRUG LABEL: OPITOX TOPICAL
NDC: 72380-521 | Form: GEL
Manufacturer: Vivera Pharmaceuticals, Inc.
Category: otc | Type: HUMAN OTC DRUG LABEL
Date: 20191205

ACTIVE INGREDIENTS: MENTHOL 3.5 g/100 mL; CAMPHOR (SYNTHETIC) 0.2 g/100 mL
INACTIVE INGREDIENTS: ALCOHOL; WATER; CARBOMER HOMOPOLYMER, UNSPECIFIED TYPE; GLYCERIN; CANNABIS SATIVA SEED OIL; CANNABIDIOL; ALOE VERA LEAF; ARNICA MONTANA FLOWER; PEPPERMINT OIL; SPEARMINT OIL; PROPYLENE GLYCOL; HAMAMELIS VIRGINIANA LEAF; TEA TREE OIL; PAPRIKA; GREEN TEA LEAF; PHENOXYETHANOL; CAPRYLIC ALCOHOL; ETHYLHEXYLGLYCERIN; HEXYLENE GLYCOL; TROLAMINE

OPITOX TOPICAL GEL PAIN RELIEF

DRUG FACTS

Active Ingredients
Menthol 3.5%
Camphor 0.2%

Purpose
Menthol ............................Topical Analgesic
Camphor ..........................Topical Analgesic

INDICATIONS AND USAGE

Uses: For temporary relief of minor aches and pains
of sore muscles and joints associated with:
• arthritis
• backache
• strains
• sprains

Warnings: For external use only.

OTHER SAFETY INFORMATION

Flammable: Keep away from excessive heat or open flame.

Ask a doctor before use if you have: Sensitive skin

When using this product: Avoid contact with the
eyes and/or mucous membranes; Not for ophthalmic
use; Do not apply to wounds or damaged skin; Do not
use with other sprays, ointments, creams or liniments;
Do not apply to irritated skin or if excessive irritation
develops; Do not bandage; Do not use with heating
pads or device.

Stop use and contact your physician if:
Condition worsens, irritation develops, or if symptoms
persist for more than seven (7) days, or clear up
and recur.

Keep out of reach of children: If accidentally
ingested, get medical help or contact a Poison Control
Center immediately.

PREGNANCY OR BREAST FEEDING

If pregnant or breast-feeding: Ask a health professional before use.

Directions:
Adults and Children 12 years of age and older:
Rub a thin film over affected area(s) not more than
four (4) times daily. Rinse hands with cool water after
use. Use only as directed.

Children under 12 years of age: Consult physician

OTHER INFORMATION: Store in a cool, dry place
with lid closed tightly.

Inactive Ingredients: SD Alcohol 40-B, Water,
Carbomer, Glycerin, Cannabis Sativa (Hemp) Seed Oil,
Cannabidiol (CBD), Aloe Barbadensis Leaf Juice, Arnica
Montana Flower Extract, Mentha Piperita (Peppermint)
Oil, Mentha Viridis (Spearmint) Leaf Oil, Propylene
Glycol, Hamamelis Virginiana (Witch Hazel) Extract,
Melaleuca Alternifolia (Tea Tree) Leaf Oil, Capsicum
Annuum Fruit Extract, Camellia Sinensis (Green
Tea) Leaf Extract, Phenoxyethanol, Caprylyl Glycol,
Ethylhexylglycerin, Hexylene Glycol, Triethanolamine

Questions or Comments: 1-844-484-8372

Principal Display Package

NDC# 72380-521-10

soba®
medical

OPITOX®
TOPICAL GEL

PAIN RELIEF

BOX CONTAINS:
3 FL OZ (88.7mL)
TOPICAL GEL

6 16728 00059 0

SUGGESTED USE:
Adults and Children 12 years of age
and older: Rub a thin film over affected
area(s) not more than four (4) times
daily. Rinse hands with cool water after
use. Use only as directed.
Children under 12 years of age:
Consult physician.

WARNINGS: Do not exceed
suggested use. This product is not
intended for pregnant or lactating
mothers. All individuals should consult
with a health practitioner prior to use.
If you experience any adverse reactions
after use, please discontinue and
consult your doctor. Keep out of reach
of children. Not for ophthalmic use.

soba®
medical

Manufactured for:
Soba Medical
A subsidiary of Vivera Pharmaceuticals
11100 Greenstone Ave. Santa Fe Springs, CA 90670
www.opitox.com

MADE IN USA REV11202019

soba®
medical

OPITOX®
TOPICAL GEL

Retail Box

Tube

Information Insert

res